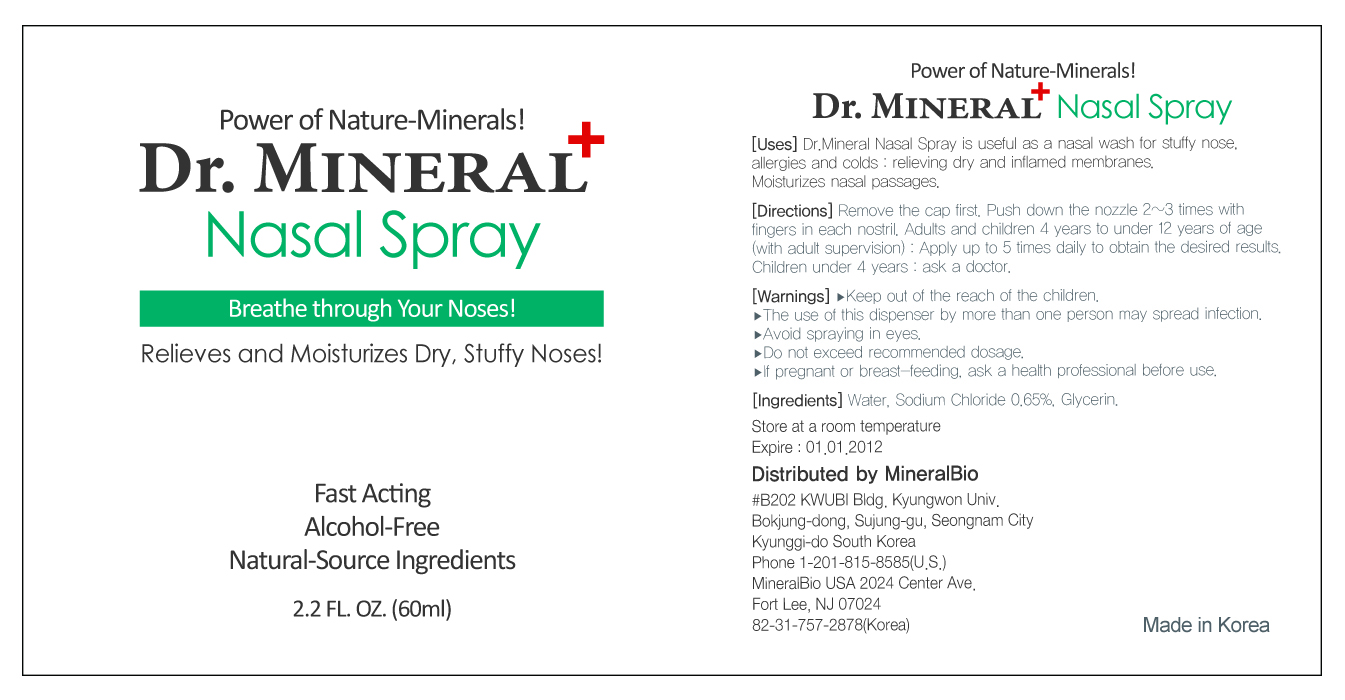 DRUG LABEL: Dr MINERAL Nasal Spray
NDC: 50499-100 | Form: SPRAY
Manufacturer: MineralBio
Category: otc | Type: HUMAN OTC DRUG LABEL
Date: 20100128

ACTIVE INGREDIENTS: SODIUM CHLORIDE 0.39 mL/60 mL
INACTIVE INGREDIENTS: WATER 59.31 mL/60 mL; GLYCERIN 0.3 mL/60 mL

[Uses]
Dr. Mineral Nasal Spray is useful as a nasal wash for stuffy nose, allergies and colds: relieving dry and inflamed membranes. Moisturizes nasal passages

[Directions]
Remove the cap first. Push down the nozzle 2-3 times with fingers in each nostril. Adults and children 4 years to under 12 years of age (with adult supervision): Apply up to 5 times daily to obtain the desired results. Children under 4 years: ask a doctor

[Warnings]
- The use of this dispenser by more than one person may spread infection
- Avoid spraying in eyes
- Do not exceed recommended dosage
- If pregnant or breast-feeding, ask a health professional before use

Keep out of reach of the children

ACTIVE INGREDIENT

[Ingredients} Water, Sodium Chloride 0.65%, Glycerin

[Storage]
Store at a room temperature